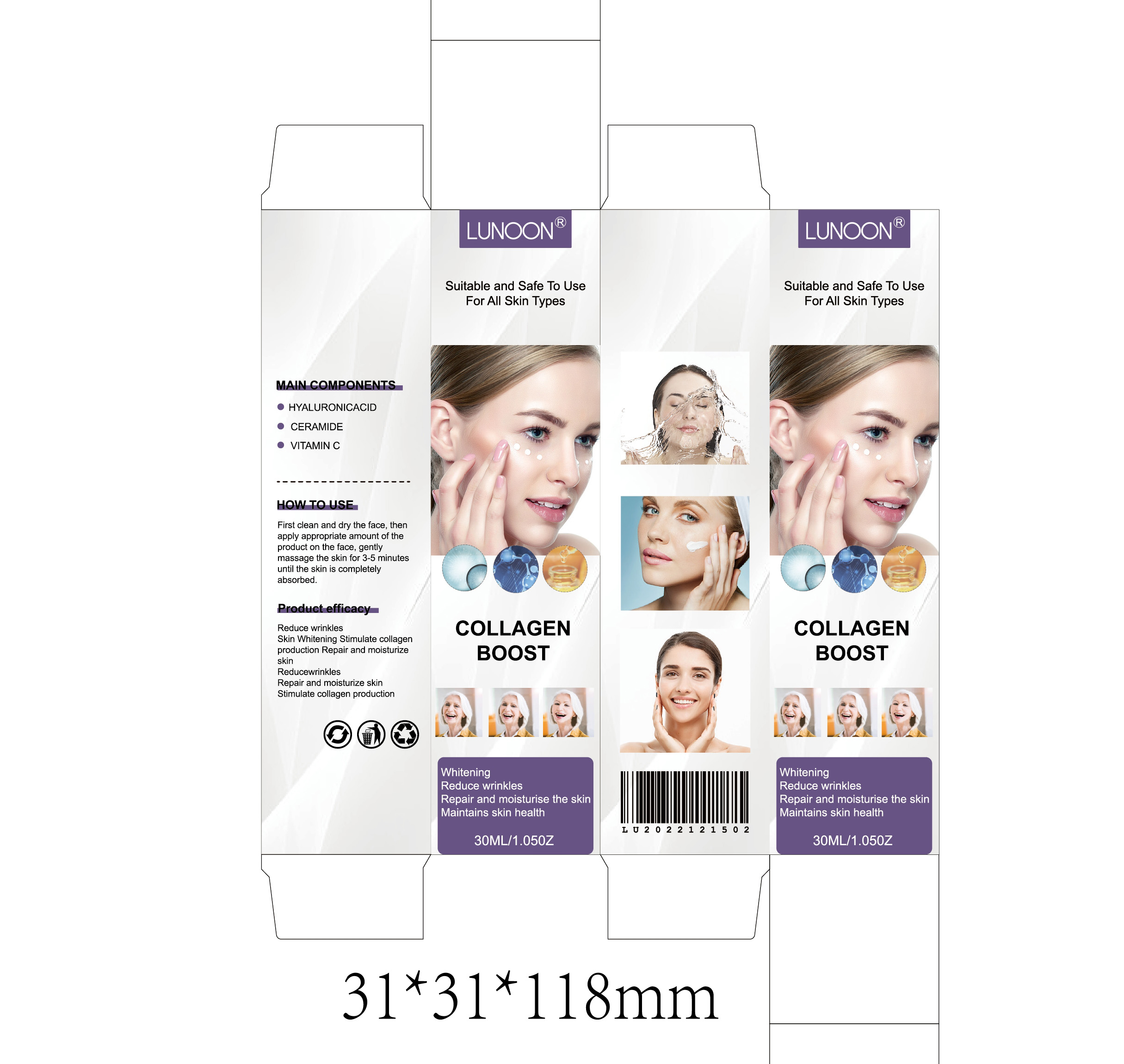 DRUG LABEL: COLLAGEN BOOST
NDC: 84732-012 | Form: CREAM
Manufacturer: Dongguan Haiyi Technology Co.,Ltd.
Category: otc | Type: HUMAN OTC DRUG LABEL
Date: 20240925

ACTIVE INGREDIENTS: HYALURONIC ACID 1 mg/30 mL
INACTIVE INGREDIENTS: ASCORBIC ACID; CERAMIDE 1

Active ingredient

HYALURONIC ACID

Inactive ingredient

CERAMIDE
VITAMIN C

Purpose section

Reduce wrinkles Skin Whitening Stimulate collagen production Repair and moisturize skin Reduce wrinklesRepair and moisturize skin Stimulate collagen production

Warning

1).For external use only, avoid directcontact with eyes, lf you feel any discomfort, stop using itand wash it with plenty of water. In severe cases, pleaseseek medical attention in time.
2). Not allowed to be used ondamaged skin,

stop use

This product may cause allergic reactions in asmall number of people.
lf youexperience any discomfort,please stop using it immediately.

not use

Not suitable for use by children, pregnantor breastfeeding people.

OUT OF CHILDREN

KEEP THE PRODUCT OUT OF REACH OF CHILDREN to

HOW TO USE

First clean and dry the face, then apply appropriate amount of the product on the face, gently massage the skin for 3-5 minutesuntil the skin is completely absorbed.

Dosage

take an appropriateamount,Use 2-3 times a week